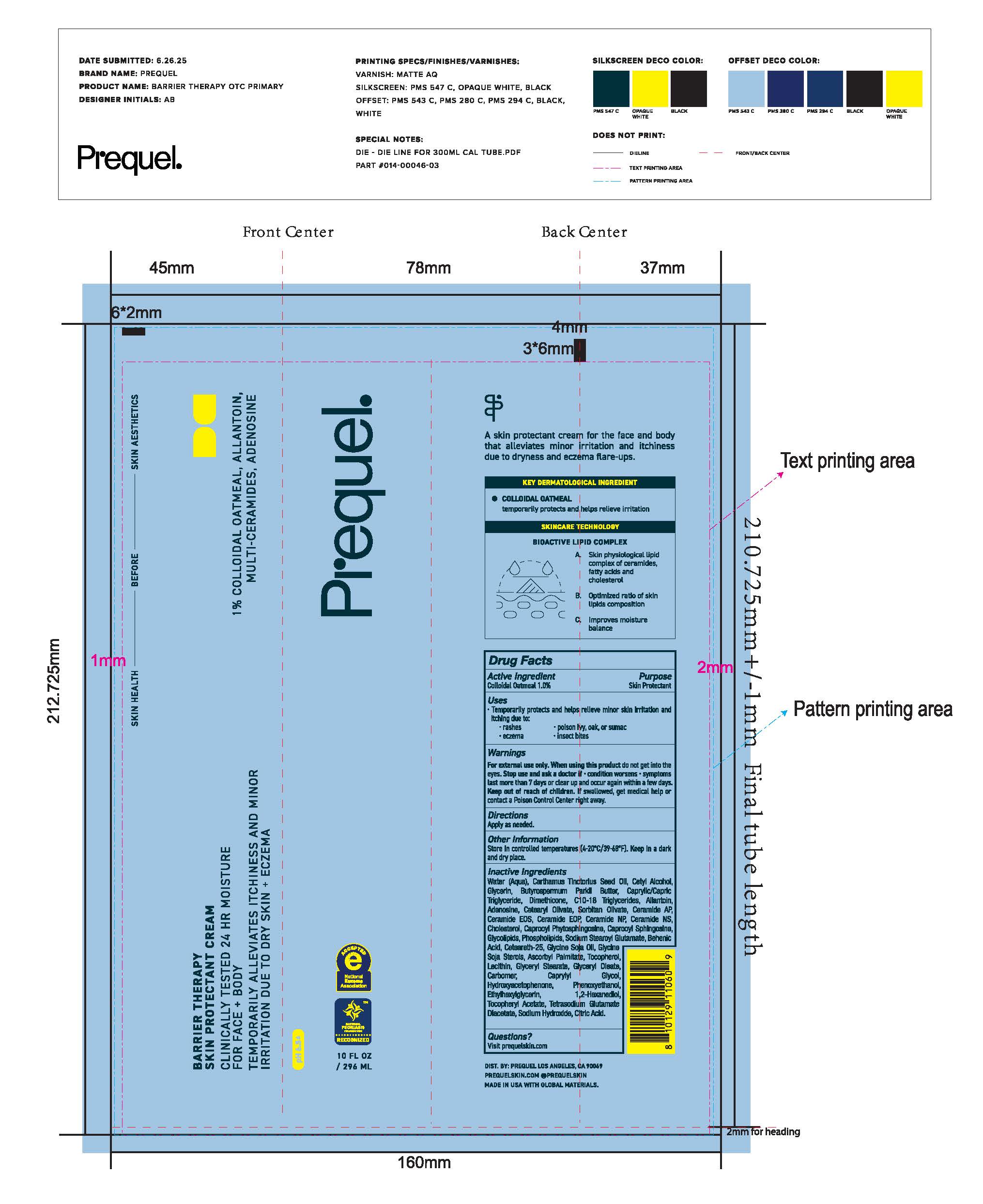 DRUG LABEL: Prequel Barrier Therapy Rich Skin Protectant Cream
NDC: 82800-100 | Form: CREAM
Manufacturer: The Center Brands, LLC
Category: otc | Type: HUMAN OTC DRUG LABEL
Date: 20251213

ACTIVE INGREDIENTS: OATMEAL 1 mg/1 g
INACTIVE INGREDIENTS: ALLANTOIN; CAPROOYL PHYTOSPHINGOSINE; ASCORBYL PALMITATE; LECITHIN, SOYBEAN; GLYCERYL STEARATE; ETHYLHEXYLGLYCERIN; GLYCERIN; WATER; CARTHAMUS TINCTORIUS WHOLE; CETYL ALCOHOL; CAPRYLIC/CAPRIC TRIGLYCERIDE; DIMETHICONE; BUTYROSPERMUM PARKII (SHEA) BUTTER; CETEARYL OLIVATE; C10-18 TRIGLYCERIDES; PHENOXYETHANOL; SORBITAN OLIVATE; TETRASODIUM GLUTAMATE DIACETATE; CITRIC ACID ACETATE; SODIUM HYDROXIDE; CERAMIDE AP; LACTIC ACID; ADENOSINE; GLYCINE SOJA (SOYBEAN) SEED; CARBOMER; HYDROXYACETOPHENONE; CERAMIDE NS; CAPROOYL SPHINGOSINE; SODIUM STEAROYL GLUTAMATE; CERAMIDE NP; BEHENIC ACID; CHOLESTEROL; CETEARETH-25; .ALPHA.-TOCOPHEROL; GLYCERYL OLEATE; CERAMIDE EOS; GLYCINE SOJA (SOYBEAN) STEROLS

Prequel Barrier Therapy Rich Skin Protectant Cream

Purpose

Skin Protectant

Active Ingredients

Colloidal Oatmeal 1.0%

Uses

Temporarily protects and helps releive minor skin irritation and itching due to:

-rashes

-eczema

-poison ivy, oak, or sumac

-insect bites

Warnings

Fox external use only.

When using this product do not get into eyes

Stop use and ask a doctor if condition worsens

symptoms last more than 7 days or clear up and occur again within a few days

If swallowed, get medial help or contact a Poison Control Center right away.

Keep out of reach of children.

Directions

Apply as needed.

Inactive ingredients

Water (Aqua), Carthamus Tinctorius (Safflower) Seed Oil, Cetyl Alcohol, Glycerin, Caprylic/Capric Triglyceride, Dimethicone, Butyrospermum Parkii (Shea) Butter, Cetearyl Olivate, C10-18 Triglycerides, Sorbitan Olivate, Adenosine, Allantoin, Behenyl/Oleyl Behenate/Oleate Esters, Ceramide NP, Ceramide NS, Ceramide AP, Ceramide EOP, Ceramide EOS, Cholesterol, Caprooyl Phytosphingosine, Caprooyl Sphingosine, Phospholipids, Glycolipids, Sodium Stearoyl Glutamate, Behenic Acid, Ceteareth-25, Glycine Soja (Soybean) Oil, Glycine Soja (Soybean) Sterols, Ascorbyl Palmitate, Tocopherol, Lecithin, Glyceryl Stearate, Glyceryl Oleate, Carbomer, hydroxyacetophenone, Phenoxyethanol, Ethylhexylglycerin, Tocopheryl Acetate, Tetrasodium Glutamate Diacetate, Sodium Chloride, Lactic Acid, Sodium Hydroxide, Citric Acid.

Other Information

Store in controlled temperatures (4-20C/39-68F). Keep in a dark and dry place,

Questions?

Visit prequelskin.com